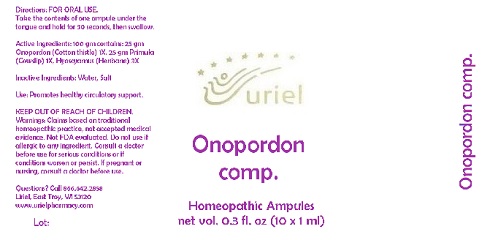 DRUG LABEL: Onopordon Comp.
NDC: 48951-7092 | Form: LIQUID
Manufacturer: Uriel Pharmacy Inc.
Category: homeopathic | Type: HUMAN OTC DRUG LABEL
Date: 20180427

ACTIVE INGREDIENTS: ONOPORDUM ACANTHIUM FLOWER 1 [hp_X]/1 mL; PRIMULA VERIS FLOWER 1 [hp_X]/1 mL; HYOSCYAMUS NIGER LEAF 3 [hp_X]/1 mL
INACTIVE INGREDIENTS: WATER; SODIUM CHLORIDE

Onopordon Comp.

INDICATIONS AND USAGE

Directions: FOR ORAL USE.

DOSAGE AND ADMINISTRATION

Take the contents of one ampule under the tongue and hold for 30 seconds, then swallow

ACTIVE INGREDIENT

Active Ingredients: 100 gm contains: 25 gm Onopordon (Cotton thistle) 1X, 25 gm Primula (Cowslip) 1X, Hyoscyamus (Henbane) 3X

Inactive Ingredients: Water, Salt

PURPOSE

Use: Promotes healthy circulatory support.

KEEP OUT OF REACH OF CHILDREN.

WARNINGS

Warnings: Claims based on traditional homeopathic practice, not accepted medical evidence. Not FDA evaluated. Do not use if allergic to any ingredient. Consult a doctor before use for serious conditions or if conditions worsen or persist. If pregnant or nursing, consult a doctor before use.

QUESTIONS

Questions? Call 866.642.2858 Uriel, East Troy, WI 53120 www.urielpharmacy.com